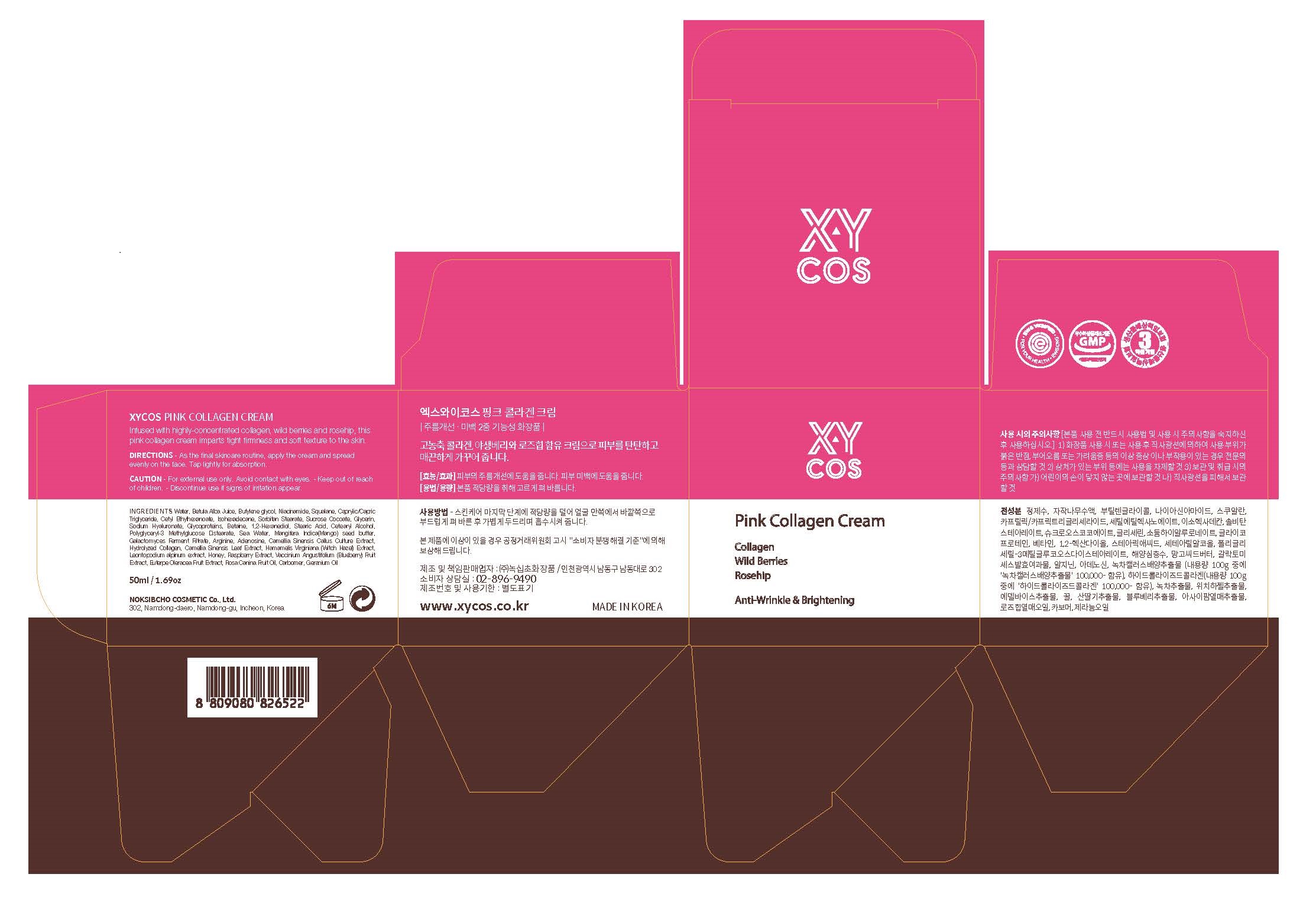 DRUG LABEL: XYCOS PINK COLLAGENCREAM
NDC: 73590-0052 | Form: CREAM
Manufacturer: NOKSIBCHO cosmetic Co., Ltd.
Category: otc | Type: HUMAN OTC DRUG LABEL
Date: 20200417

ACTIVE INGREDIENTS: ADENOSINE 0.04 g/100 mL; NIACINAMIDE 2 g/100 mL
INACTIVE INGREDIENTS: WATER

Drug Facts

ACTIVE INGREDIENT

adenosine, niacinamide

INACTIVE INGREDIENT

Aqua
Butylene Glycol
Betula Platyphylla Japonica Juice
Squalane
Caprylic/Capric Triglyceride
Cetyl Ethylhexanoate
Isohexadecane
palmitic Acid
Sorbitan Stearate
1,2-Hexanediol
Glycerin
Stearic Acid
Polyglyceryl-3 Methylglucose Distearate
Sea Water
Mangifera Indica (Mango) seed butter
Arginine
Sucrose Cocoate
GERANIUM OIL
Rosa Canina Fruit Oil
Polyacrylic acid
Phenoxy ethanol
Galactomyces Ferment Filtrate
Propylene Glycol
Myristic Acid
Sodium Hyaluronate
Camellia Sinensis Callus Culture Extract
Disodium EDTA
Ethylhexylglycerin
Methyl Paraben
Leontopodium alpinum extract
Caprylyl Glycol
Camellia Sinensis Leaf Extract
Hamamelis Virginiana (Witch Hazel) Extract
Hydrolyzed Collagen
Vaccinium Angustifolium (Blueberry) Fruit Extract
Euterpe Oleracea Fruit Extract
Tropolone

PURPOSE

anti-wrinkle & brightening

keep out of reach of the children

INDICATIONS AND USAGE

apply proper amount to the skin

WARNINGS

For external use only
When using this product

■ if the following symptoms occurs after use, stop use and consult with a skin specialist

red specks, swelling, itching

■ don’t use on the part where there is injury, eczema, or dermatitis

Keep out of reach of children

■ if swallowed, get medical help or contact a person control center immediately